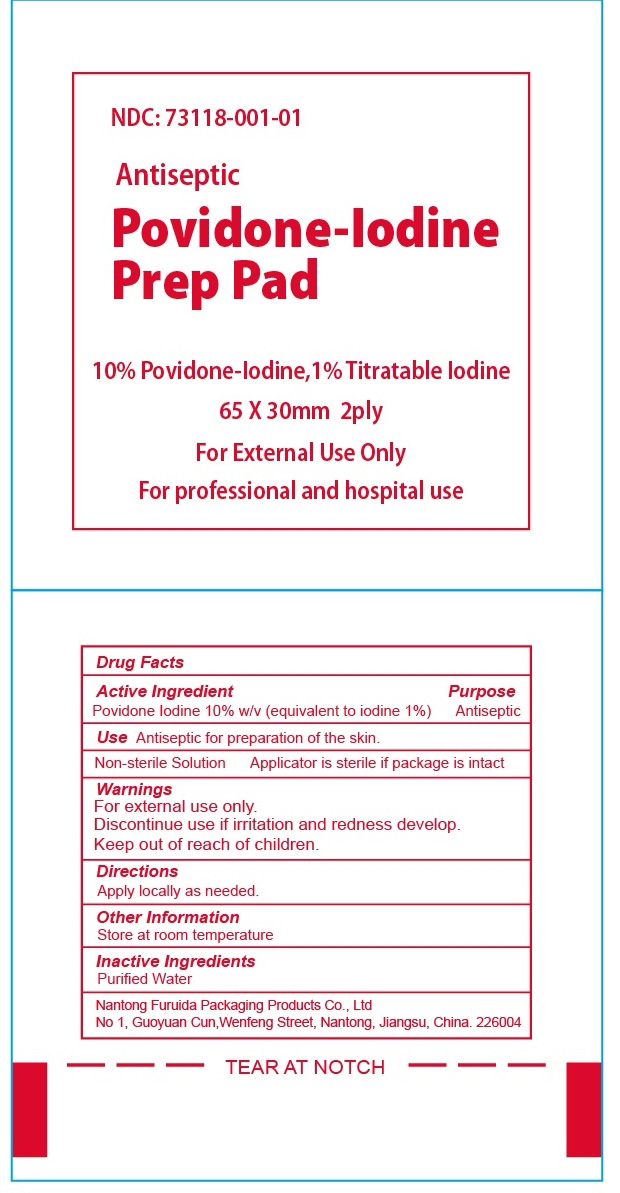 DRUG LABEL: Povidone-Iodine Prep Pad
NDC: 73118-001 | Form: SWAB
Manufacturer: Nantong Furuida Packaging Products Co., Ltd.
Category: otc | Type: HUMAN OTC DRUG LABEL
Date: 20210524

ACTIVE INGREDIENTS: POVIDONE-IODINE 10 mg/1 1
INACTIVE INGREDIENTS: WATER

731180--001

Active Ingredient

POVIDONE-IODINE 10% W/v (equivalent to iodine 1%)

Purpose

Antiseptic

Warnings

For External use only.
Discontinue use if irritation and redness develop

Keep out of reach of children

Directions

Apple locally as needed.

Other information

Store at room temperature:59o-86oF(15--30℃)

Use

Antiseptic for preparation of the skin

Inactive Ingredients

Purified Water